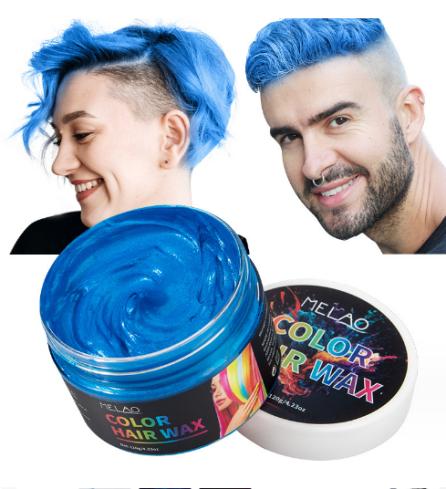 DRUG LABEL: MELAO COLOR HAIR WAX
NDC: 83566-583 | Form: CREAM
Manufacturer: Guangzhou Yilong Cosmetics Co., Ltd
Category: otc | Type: HUMAN OTC DRUG LABEL
Date: 20240820

ACTIVE INGREDIENTS: PHENOXYETHANOL 10 g/100 g
INACTIVE INGREDIENTS: WATER O-15 65 g/100 g; GLYCERIN 25 g/100 g

MELAO COLOR HAIR WAX

Active ingredients

Phenoxyethanol 10%

Inactive ingredients

Water 65%

Glycerin 25%

Purpose

Hair dyeing and coloring

Uses

Step 1: Clean and dry hair
Step 2: Take out an appropriate amount of paste
Step 3: Apply evenly to the hair that needs to be colored

Warning

For external use only.

Stop use and ask a doctor if

rash occurs.

Do not use

on damaged or broken skin.

When using this product

keep out of eyes. Rinse withwater to remove.

keep out of eyes. Rinse withwater to remove.

If swallowed, get medical help or contact a Poison Control Center right away.

DOSAGE & ADMINISTRATION

Squeeze out an appropriate amount of product and spread evenly on hair